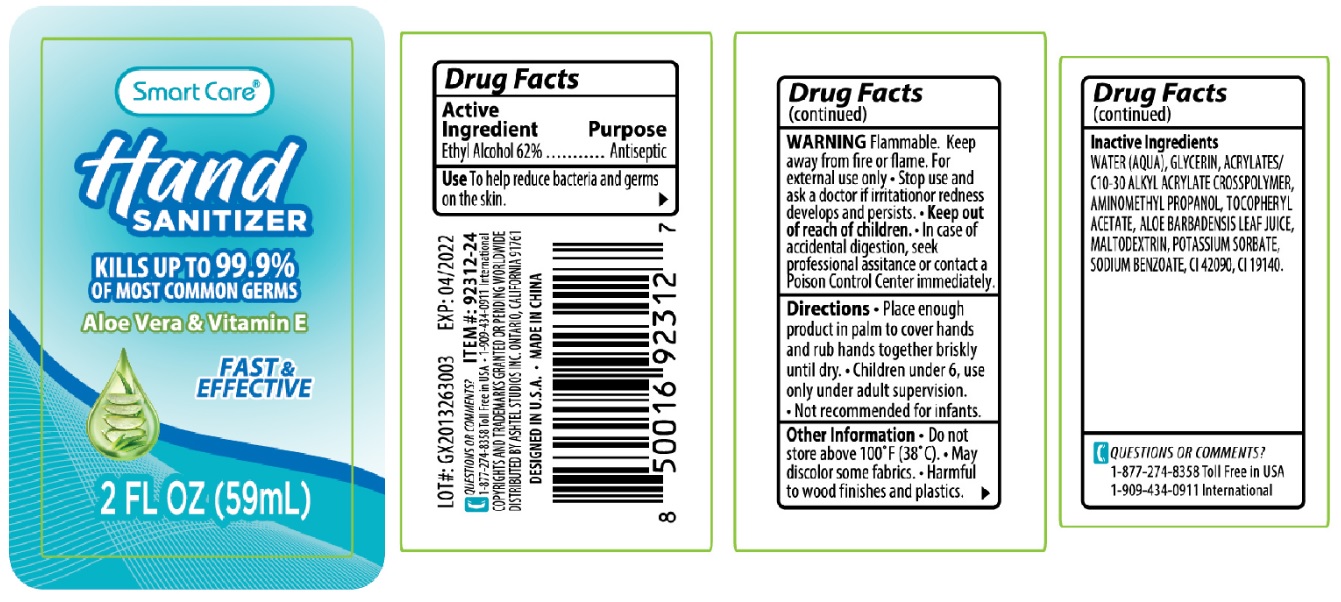 DRUG LABEL: Smart Care Hand Sanitizer 2 oz
NDC: 70108-051 | Form: GEL
Manufacturer: Ashtel Studios, Inc
Category: otc | Type: HUMAN OTC DRUG LABEL
Date: 20200423

ACTIVE INGREDIENTS: ALCOHOL 62 mL/100 mL
INACTIVE INGREDIENTS: WATER; GLYCERIN; CARBOMER INTERPOLYMER TYPE A (ALLYL SUCROSE CROSSLINKED); AMINOMETHYLPROPANOL; .ALPHA.-TOCOPHEROL ACETATE; ALOE VERA LEAF; MALTODEXTRIN; POTASSIUM SORBATE; SODIUM BENZOATE; FD&C BLUE NO. 1; FD&C YELLOW NO. 5

Smart Care® Hand SANITIZER

Active Ingredient

Ethyl Alcohol 62%

Purpose

Antiseptic

Use

To help reduce bacteria and germs on the skin.

WARNING

Flammable. Keep away from fire or flame. For external use only

• Stop use and ask a doctor if irritation or redness develops and persists.

• Keep out of reach of children. • In case of accidental digestion, seek professional assistance or contact a Poison Control Center immediately.

Directions

• Place enough product in palm to cover hands and rub hands together briskly until dry.

• Children under 6, use only under adult supervision.

• Not recommended for infants.

Other Information

•Do not store above 100° F (38°C).

• May discolor some fabrics.

• Harmful to wood finishes and plastics.

Inactive Ingredients

WATER(AQUA), GLYCERIN, ACRYLATES/C10-30 ALKYL ACRYLATE CROSSPOLYMER, AMINOMETHYLPROPANOL, TOCOPHERYL ACETATE, ALOE BARBADENSIS LEAF JUICE, MALTODEXTRIN, POTASSIUM SORBATE, SODIUM BENZOATE, CI 42090, CI 19140

QUESTIONS OR COMMENTS?

1-877-274-8358 Toll Free in USA

1-909-434-0911 International

KILLS UP TO 99.9% OF MOST COMMON GERMS

Aloe Vera & Vitamin E

FAST & EFFECTIVE

COPYRIGHTS AND TRADEMARKS GRANTED OR PENDING WORLDWIDE

DISTRIBUTED BY ASHTEL STUDIOS INC. ONTARIO, CALIFORNIA 91761

DESIGNED IN U.S.A. • MADE IN CHINA